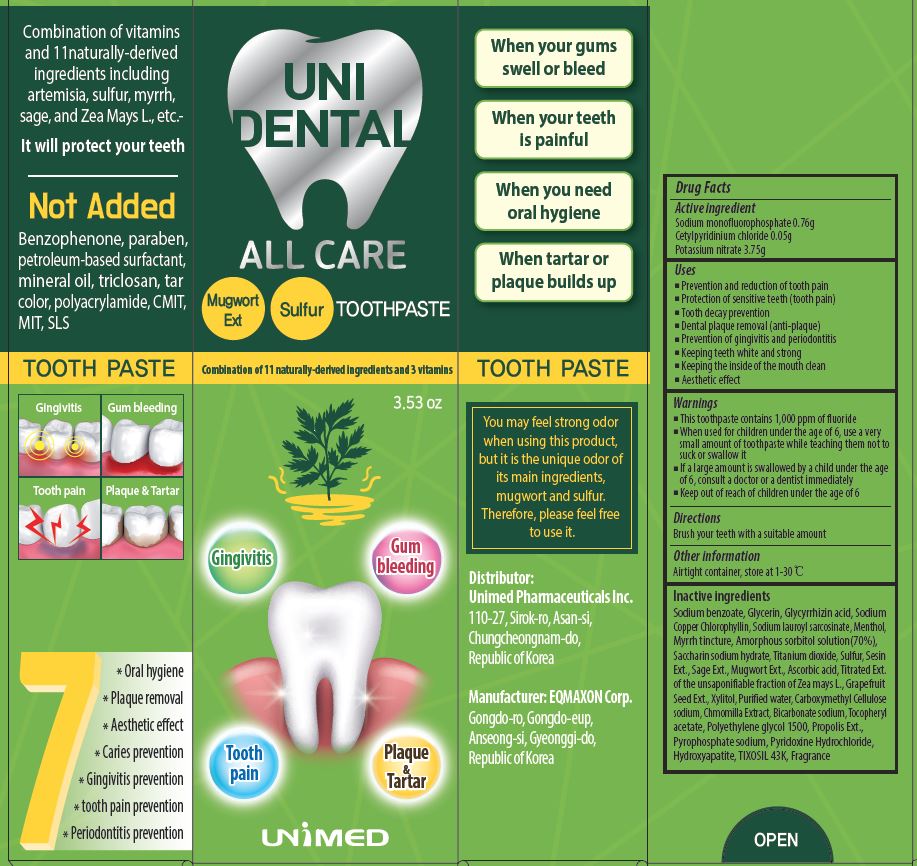 DRUG LABEL: Unidental All CareToothpaste
NDC: 73669-012 | Form: PASTE, DENTIFRICE
Manufacturer: Unimed Pharmaceuticals, Inc.
Category: otc | Type: HUMAN OTC DRUG LABEL
Date: 20230420

ACTIVE INGREDIENTS: POTASSIUM NITRATE 3.75 g/100 g; SODIUM MONOFLUOROPHOSPHATE 0.76 g/100 g; CETYLPYRIDINIUM CHLORIDE 0.3 g/100 g
INACTIVE INGREDIENTS: WATER

Drug Facts

ACTIVE INGREDIENT

Sodium monofluorophosphate, Cetylpyridinium chloride, Potassium nitrate

INACTIVE INGREDIENT

Sodium benzoate, Glycerin, Glycyrrhizin acid, Sodium
Copper Chlorophyllin, Sodium lauroyl sarcosinate, Menthol,
Myrrh tincture, Amorphous sorbitol solution(70%),
Saccharin sodium hydrate, Titanium dioxide, Sulfur, Sesin
Ext., Sage Ext., Mugwort Ext., Ascorbic acid, Titrated Ext.
of the unsaponifiable fraction of Zea mays L., Grapefruit
Seed Ext., Xylitol, Purified water, Carboxymethyl Cellulose
sodium, Chmomilla Extract, Bicarbonate sodium, Tocopheryl
acetate, Polyethylene glycol 1500, Propolis Ext.,
Pyrophosphate sodium, Pyridoxine Hydrochloride,
Hydroxyapatite, TIXOSIL 43K, Fragrance

PURPOSE

■ Prevention and reduction of tooth pain
■ Protection of sensitive teeth (tooth pain)
■ Tooth decay prevention
■ Dental plaque removal (anti-plaque)
■ Prevention of gingivitis and periodontitis
■ Keeping teeth white and strong
■ Keeping the inside of the mouth clean
■ Aesthetic effect

keep out of reach of the children

INDICATIONS AND USAGE

Brush your teeth with a suitable amount

WARNINGS

■ This toothpaste contains 1,000 ppm of fluoride
■ When used for children under the age of 6, use a very
small amount of toothpaste while teaching them not to
suck or swallow it
■ If a large amount is swallowed by a child under the age
of 6, consult a doctor or a dentist immediately
■ Keep out of reach of children under the age of 6

DOSAGE AND ADMINISTRATION

dental use only